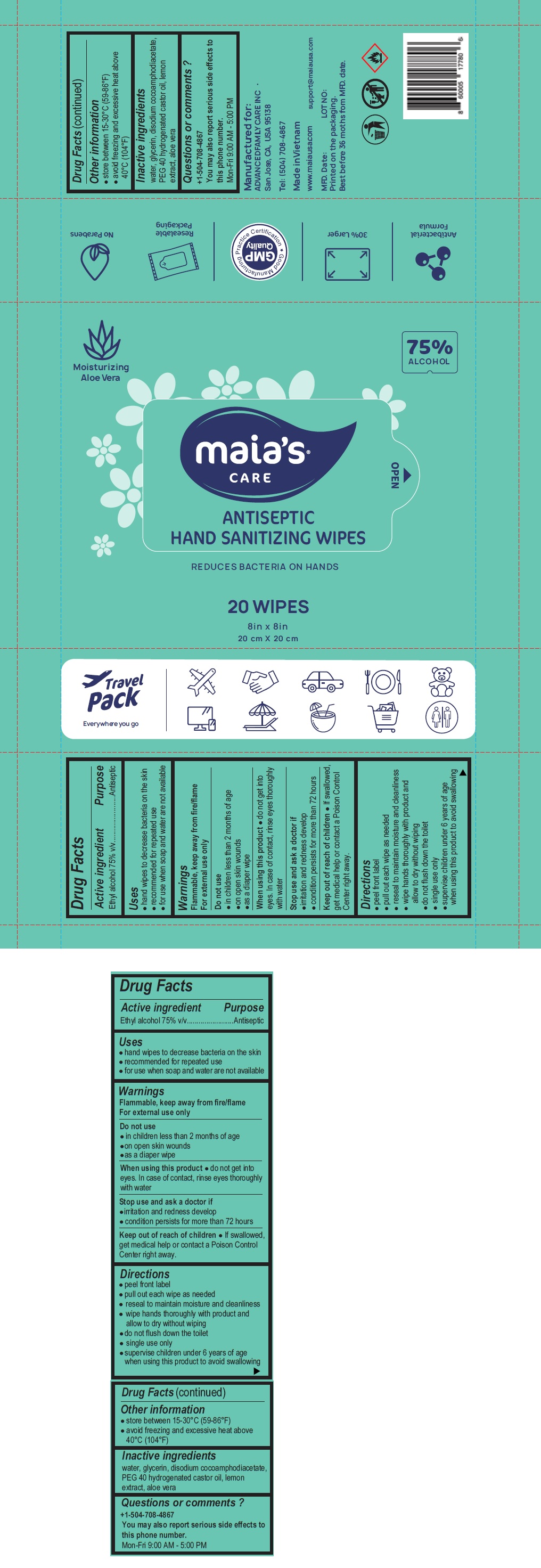 DRUG LABEL: Maias CARE ANTISEPTIC HAND SANITIZING WIPES
NDC: 78898-975 | Form: CLOTH
Manufacturer: Eco Wipes Vietnam Corporation
Category: otc | Type: HUMAN OTC DRUG LABEL
Date: 20200917

ACTIVE INGREDIENTS: ALCOHOL 75 mL/100 mL
INACTIVE INGREDIENTS: WATER; GLYCERIN; DISODIUM COCOAMPHODIACETATE; POLYOXYL 40 HYDROGENATED CASTOR OIL; LEMON; ALOE VERA LEAF

Maia's ®CARE ANTISEPTIC HAND SANITIZING WIPES

Active ingredient

Ethyl alcohol 75% v/v

Purpose

Antiseptic

Uses

- hand wipes to decrease bacteria on the skin
- recommended for repeated use
- for use when soap and water are not available

Warnings

Flammable, keep away from fire/flame
For external use only

Do not use

- in children less than 2 months of age
- on open skin wounds
- as a diaper wipe

When using this product ● do not get into eyes. In case of contact, rinse eyes thoroughly with water

Stop use and ask a doctor if

- irritation and redness develop
- condition persists for more than 72 hours

Keep out of reach of children ● If swallowed, get medical help or contact a Poison Control Center right away.

Directions

- peel front label
- pull out each wipe as needed
- reseal to maintain moisture and cleanliness
- wipe hands thoroughly with product and allow to dry without wiping
- do not flush down the toilet
- single use only
- supervise children under 6 years of age when using this product to avoid swallowing

Other information

- store between 15-30°C (59-86°F)
- avoid freezing and excessive heat above 40°C (104°F)

Inactive ingredients

water, glycerin, disodium cocoamphodiacetate, PEG 40 hydrogenated castor oil, lemon extract, aloe vera

Questions or comments ?

+1-504-708-4867

You may also report serious side effects to this phone number.

Mon-Fri 9:00 AM - 5:00 PM

Moisturizing Aloe Vera

REDUCES BACTERIA ON HANDS

8in x 8in

20 cm X 20 cm

Travel Pack

Everywhere you go

Antibacterial Formula

30% Larger

Good Manufacturing Practice Certification

GMP Quality

Resealable Packaging

No Parabens

Manufactured for:
ADVANCED FAMILY CARE INC .
San Jose, CA, USA 95138

Tel: (504) 708-4867

Made in Vietnam
www.maiausa.com

support@maiausa.com

Best before 36 moths from MFD. date.